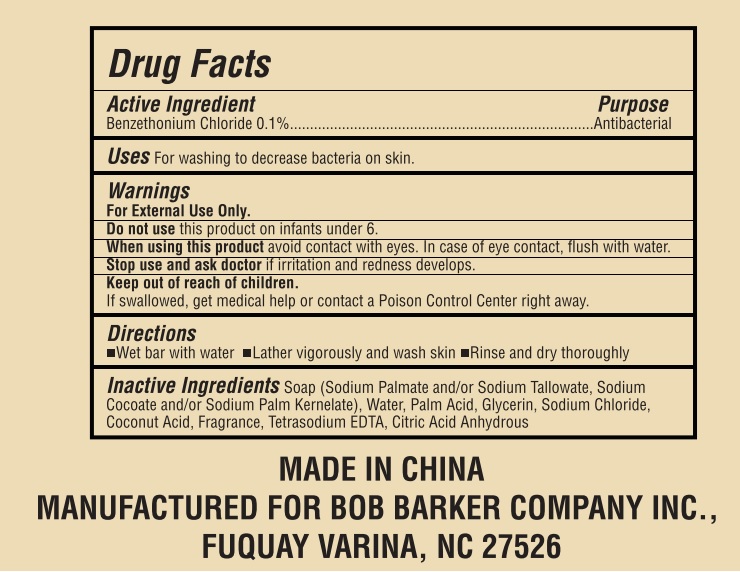 DRUG LABEL: BobBarker antibacterial wrapped body
NDC: 72797-001 | Form: SOAP
Manufacturer: Yangzhou H&R Plastic Daily Chemical Co., Ltd.
Category: otc | Type: HUMAN OTC DRUG LABEL
Date: 20241204

ACTIVE INGREDIENTS: BENZETHONIUM CHLORIDE 0.1 g/100 g
INACTIVE INGREDIENTS: WATER; PALM ACID; SODIUM CHLORIDE; COCONUT ACID; SODIUM PALMATE; SODIUM COCOATE; SODIUM PALM KERNELATE

Active Ingredient

Benzethonium Chloride 0.1%

Purpose

Antibacterial

Uses

for washing to decrease bacteria on the skin.

Warnings

For external use only.

When using this product

Avoid contact with eyes. In case of eye contact, flush with water.

Don't use this product on infants under 6 months of age.

Stop use and ask a doctor

If irritation and redness develops.

Keep out of reach of children.

If swallowed, get medical help or contact a Poison Control Center right away.

Directions

- wet bar with water
- lather vigorously and wash skin
- rinse and dry thoroughly.

Inactive Ingredients

Soap (Sodium Palmate and/or Sodium Tallowate, Sodium Cocoate and/or Sodium Palm Kernelate), Water, Palm Acid, Glycerin, Sodium Chloride, Coconut Acid, Fragrance, Tetrasodium EDTA, Citric Acid Anhydrous